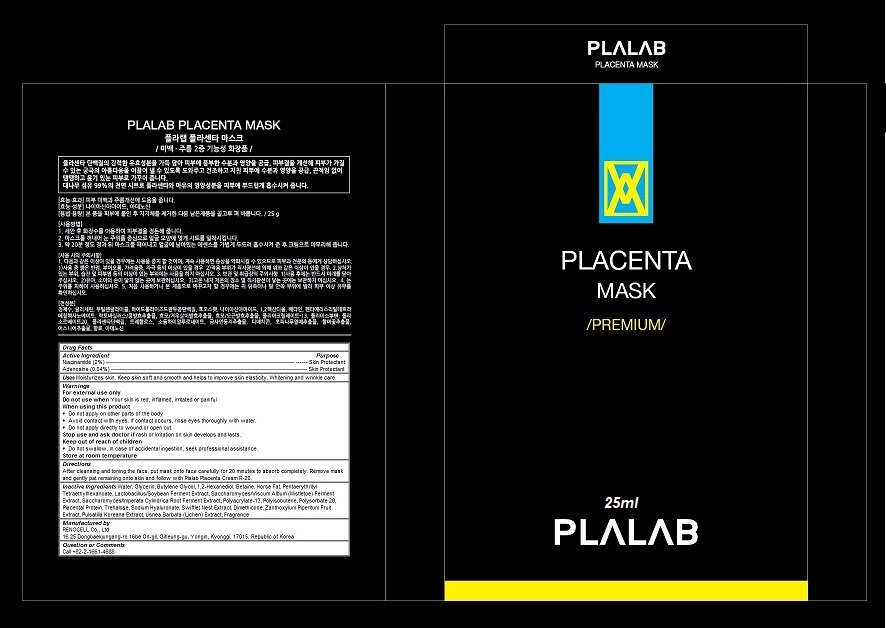 DRUG LABEL: Plalab Placenta Mask
NDC: 70326-104 | Form: PATCH
Manufacturer: RENOCELL Co., Ltd
Category: otc | Type: HUMAN OTC DRUG LABEL
Date: 20151223

ACTIVE INGREDIENTS: NIACINAMIDE 0.02 1/25 mL; ADENOSINE 0.0004 1/25 mL
INACTIVE INGREDIENTS: water; GLYCERIN; Butylene Glycol; 1,2-Hexanediol; Betaine; Pentaerythrityl Tetraethylhexanoate; POLYISOBUTYLENE (1000 MW); Polysorbate 20; SUS SCROFA PLACENTA; Trehalose; HYALURONATE SODIUM; Dimethicone; ZANTHOXYLUM PIPERITUM FRUIT PULP; PULSATILLA KOREANA ROOT; USNEA BARBATA

Plalab Placenta Mask